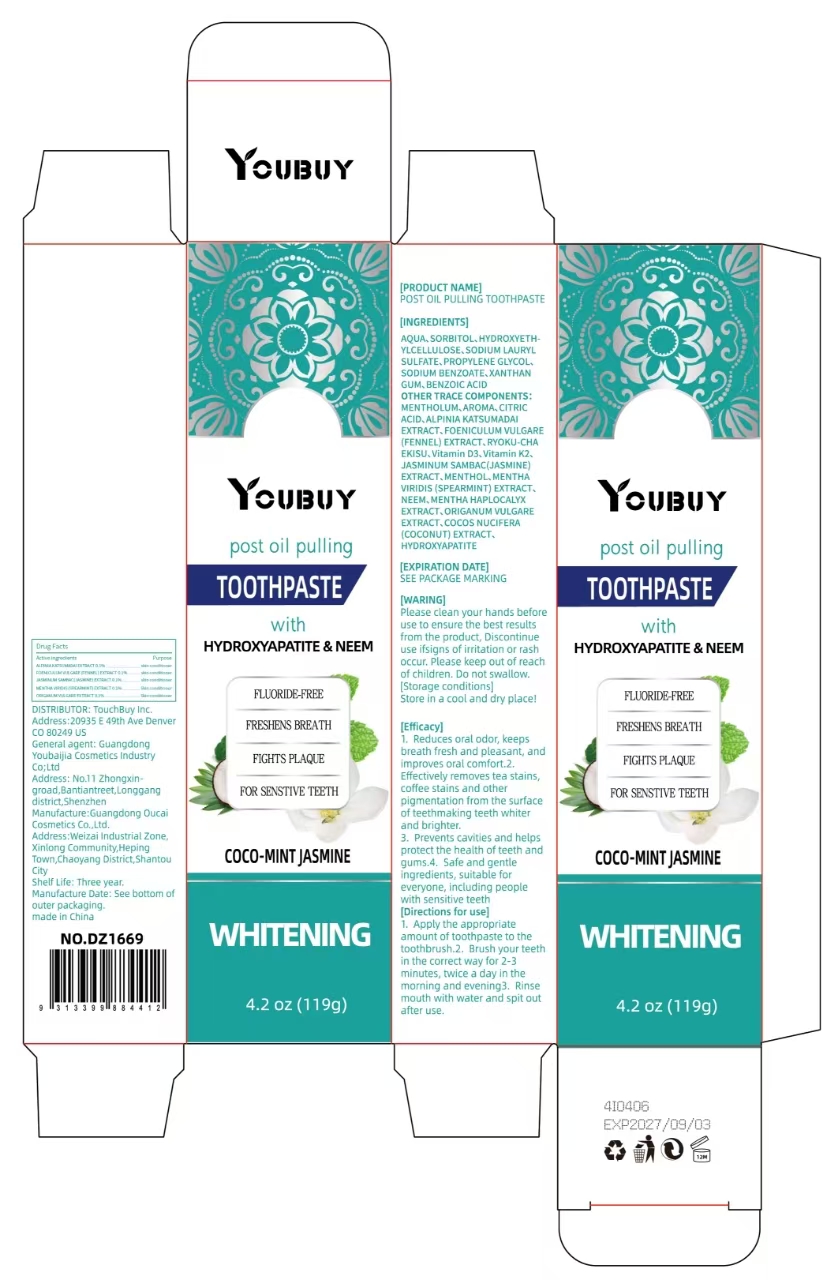 DRUG LABEL: YOUBUY post oil pulling tooth-paste
NDC: 84712-029 | Form: PASTE
Manufacturer: Guangdong Youbaijia Cosmetic Industry Co., Ltd
Category: otc | Type: HUMAN OTC DRUG LABEL
Date: 20241028

ACTIVE INGREDIENTS: JASMINUM SAMBAC WHOLE 0.119 g/119 g; ORIGANUM VULGARE LEAF OIL 0.119 g/119 g; FOENICULUM VULGARE (FENNEL) SEED EXTRACT 0.119 g/119 g; MENTHA VIRIDIS (SPEARMINT) LEAF OIL 0.119 g/119 g; ALPINIA KATSUMADAI SEED EXTRACT 0.119 g/119 g
INACTIVE INGREDIENTS: SORBITOL 0.119 g/119 g

ACTIVE INGREDIENT

ALPINIA KATSUMADAI EXTRACT 0.1%
FOENICULUM VULGARE (FENNEL) EXTRACT 0.1%
JASMINUM SAMBAC(JASMINE) EXTRACT 0.1%
MENTHA VIRIDIS (SPEARMINT) EXTRACT 0.1%
ORIGANUM VULGARE EXTRACT 0.1%

INACTIVE INGREDIENT

AQUA
SORBITOL
HYDROXYETHYLCELLULOSE
SODIUM LAURYL SULFATE
PROPYLENE GLYCOL
SODIUM BENZOATE
XANTHAN GUM
BENZOIC ACID
MENTHOLUM
AROMA
CITRIC ACID
RYOKU-CHA EKISU
Vitamin D3
Vitamin K2
MENTHOL
MENTHA VIRIDIS (SPEARMINT) EXTRACT
Neem
COCOS NUCIFERA (COCONUT) EXTRACT
HYDROXYAPATITE

DO NOT USE

Discontinue use if signs of irritation or rash occur

KEEP OUT OF REACH OF CHILDREN

Please keep out of reach of children. Do not swallow.

PURPOSE

Reduces oral odor, keeps breath fresh

QUESTIONS

Contact name: Jessie Peng
Company phone number: +1 818 579 7288
Company e-mail: jessie@registeragentllc.com

STOP USE

Discontinue use if signs of irritation or rash occur

WHEN USING

keep out of eyes. Rinse with water to remove.

WARNINGS

For external use only.

STORAGE AND HANDLING

Storage conditions:Keep away from light and in a dry place.

DOSAGE AND ADMINISTRATION

[Directions for use]1. Apply the appropriate amount of toothpaste to the toothbrush.

2. Brush your teeth in the correct way for 2-3 minutes, twice a day in the morning and evening

3. Rinse mouth with water and spit outafter use.

INDICATIONS AND USAGE

[Efficacy]1. Reduces oral odor, keeps breath fresh and pleasant, and improves oral comfort.

2.Effectively removes tea stains,coffee stains and other pigmentation from the surface of teeth making teeth whiter and brighter.

3. Prevents cavities and helps protect the health of teeth and gums.

4. Safe and gentle ingredients, suitable for everyone, including people with sensitive teeth